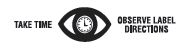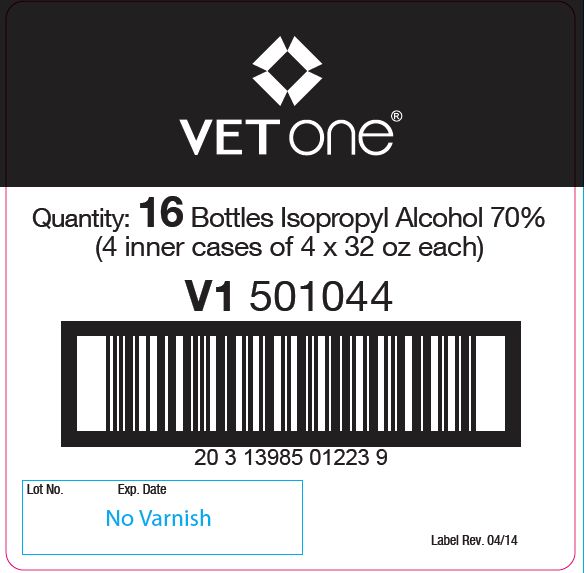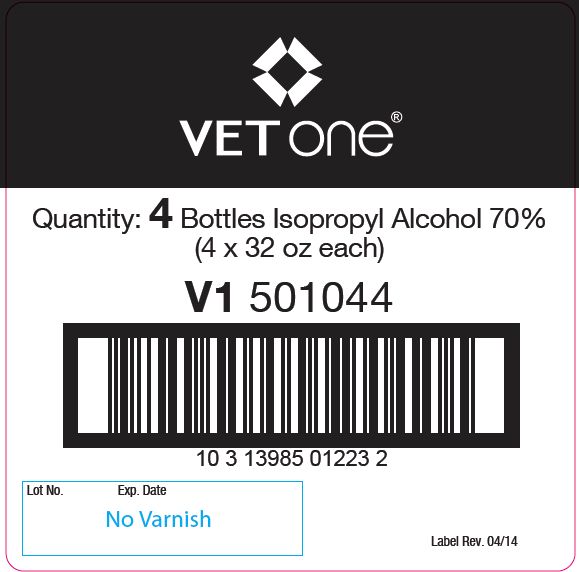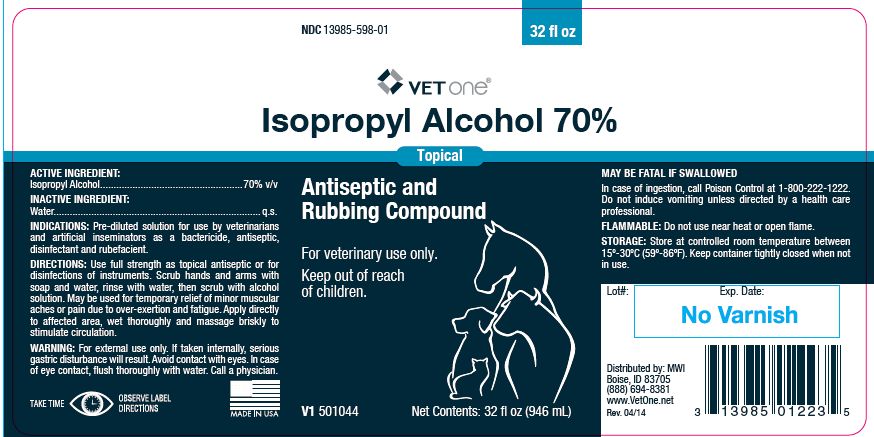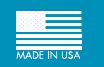 DRUG LABEL: Isopropyl Alcohol
NDC: 13985-598 | Form: LIQUID
Manufacturer: MWI/Vet One
Category: animal | Type: OTC ANIMAL DRUG LABEL
Date: 20241029

ACTIVE INGREDIENTS: ISOPROPYL ALCOHOL 557.25 g/1 L

Isopropyl Alcohol 70%

PURPOSE

Topical

Antiseptic and Rubbing Compound

For veterinary use only.

Keep out of reach of children.

ACTIVE INGREDIENT:

Isopropyl Alcohol.....................................................70% v/v

INACTIVE INGREDIENT:

Water............................................................................. q.s.

INDICATIONS:

Pre-diluted solution for use by veterinarians and artificial inseminators as a bactericide, antiseptic, disinfectant and rubefacient.

DIRECTIONS:

Use full strength as topical antiseptic or for disinfections of instruments. Scrub hands and arms with soap and water, rinse with water, then scrub with alcohol solution. May be used for temporary relief of minor muscular aches or pain due to over-exertion and fatigue. Apply directly to affected area, wet thoroughly and massage briskly to stimulate circulation.

WARNING:

For external use only. If taken internally, serious gastric disturbance will result. Avoid contact with eyes. In case of eye contact, flush thoroughly with water. Call a physician.

WARNINGS

MAY BE FATAL IF SWALLOWED

ADVERSE REACTIONS

In case of ingestion, call Poison Control at 1-800-222-1222. Do not induce vomiting unless directed by a health care professional.

FLAMMABLE:

Do not use near heat or open flame.

STORAGE:

Store at controlled room temperature between 15º-30ºC (59º-86ºF). Keep container tightly closed when not in use.

Net Contents:

32 fl oz (946 mL) V1 501044

INFORMATION FOR OWNERS/CAREGIVERS

Distributed by: MWI
Boise, ID 83705
(888) 694-8381
www.VetOne.net
Rev. 04/14